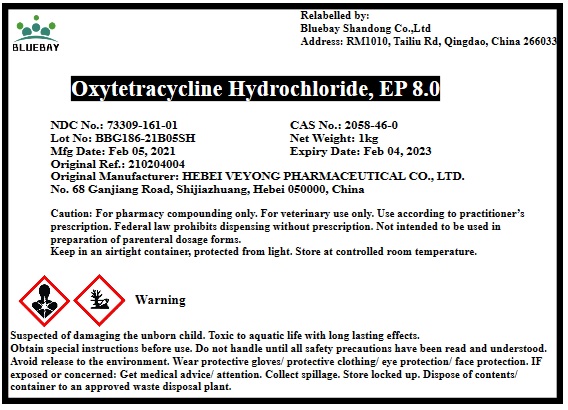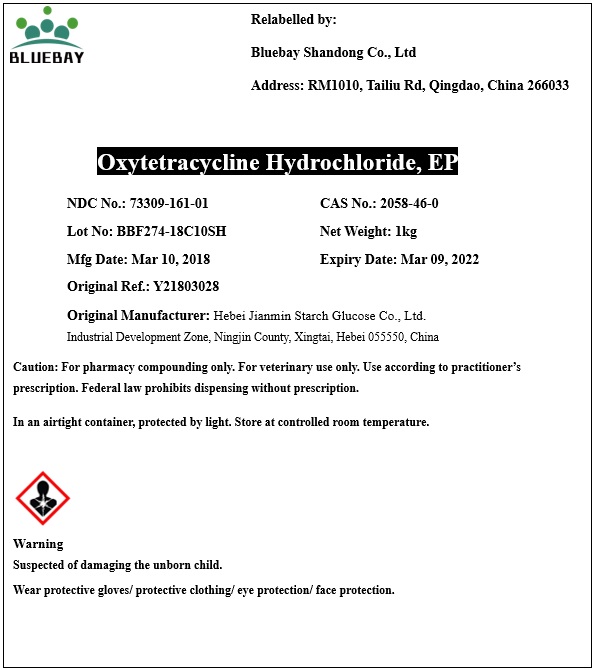 DRUG LABEL: Oxytetracycline Hydrochloride
NDC: 73309-161 | Form: POWDER
Manufacturer: BLUEBAY SHANDONG CO.,LTD
Category: other | Type: BULK INGREDIENT
Date: 20210412

ACTIVE INGREDIENTS: OXYTETRACYCLINE HYDROCHLORIDE 1 kg/1 kg

Oxytetracycline Hydrochloride